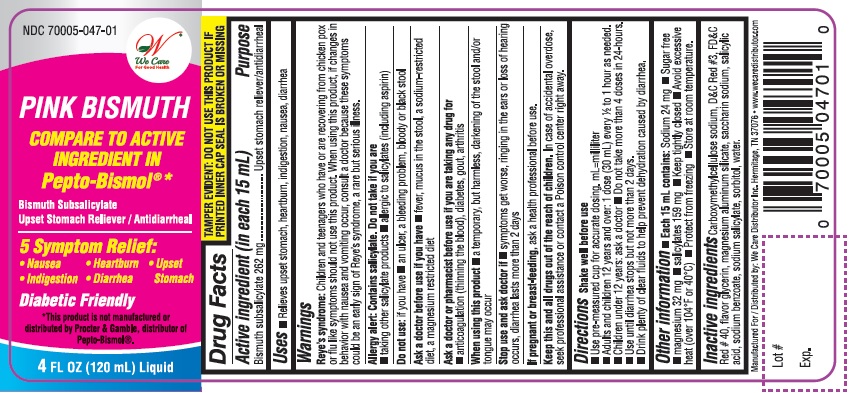 DRUG LABEL: Pink Bismuth
NDC: 70005-047 | Form: LIQUID
Manufacturer: We Care Distributor Inc.
Category: otc | Type: HUMAN OTC DRUG LABEL
Date: 20161025

ACTIVE INGREDIENTS: BISMUTH SUBSALICYLATE 262 mg/15 mL
INACTIVE INGREDIENTS: CARBOXYMETHYLCELLULOSE SODIUM; D&C RED NO. 30; FD&C RED NO. 40; GLYCERIN; MAGNESIUM ALUMINUM SILICATE; WATER; SACCHARIN SODIUM; SALICYLIC ACID; SODIUM SALICYLATE; SORBITOL; SODIUM BENZOATE

We Care Pink Bismuth Drug Facts

Active ingredient (in each 15 mL)

Bismuth subsalicylate 262 mg

Purposes

Upset stomach reliever/antidiarrheal

Uses

- relieves upset stomach, heartburn, indigestion, nausea, diarrhea

Warnings

Reye's syndrome: Children and teenagers who have or are recovering from chicken pox or flu like symptoms should not use this product. When using this product, if changes in behavior with nausea and vomitting occur, consult a doctor because these symptoms could be an early sign of Reye's syndrom, a rare but serious illness.

Allergy alert: Contains salicylates. Do not take if you are

- taking other salicylate products
- allergic to salicylates (including aspirin)

Do not use

if you have

- an ulcer, a bleeding problem, bloody or black stool

Ask a doctor before use if you have

- fever, mucus in the stool, a sodium-restricted diet, a magnesium restricted diet

Ask a doctor or pharmacist before use if you are

taking any drug for

- anticoagulation (thinning the blood), diabetes, gout, arthritis

When using this product

a temporary, but harmless, darkening of the stool and/or tongue may occur

Stop use and ask a doctor if

- symptoms get worse, ringing in the ears or loss of hearing occurs, diarrhea lasts more than 2 days

If pregnant or breast-feeding,

ask a health professional before use.

Keep this and all drugs out of the reach of children.

In case of accidental overdose, seek professional assistance or contact a Poison Control Center right away.

Directions

- Shake well before use
- Use pre-measured cup for accurate dosing. mL = mililiter
- Adults and children 12 years and over: 1 dose (30 mL) every 1/2 to 1 hour as needed
- Do not take more than 4 doses in 24 hours
- Use until diarrhea stops but not more than 2 days
- Children under 12 years: ask a doctor
- Drink plenty of clear fluids to help prevent dehydration caused by diarrhea

Other information

- Each 15 mL contains: Sodium 24 mg, Sugar free, Magnesium 32 mg
- Salicylate 159 mg
- Keep tightly closed
- Avoid excessive heat (over 104°F or 40°C)
- protect from freezing
- store at room temperature
- TEMPER EVIDENT: DO NOT USE THIS PRODUCT IF PRINTED INNER CAP SEAL IS BROKEN OR MISSING

Inactive ingredients

carboxymethylcellulose sodium, D&C red #3, FD&C red #40, flavor, glycerin, magnesium aluminum silicate, saccharin sodium, salicylic acid, sodium benzoate, sodium salicylate, sorbitol, water

Questions or comments?

1-888-705-WECARE (Mon-Fri 9am-5pm EST) or www.wecaredistributor.com

Principal Display Panel

Compare to Original Pepto-Bismol® active ingredient

ORIGINAL STRENGTH

Stomach Relief

Upset Stomach Reliever/Antidiarrheal

Bismuth Subsalicylate 262 mg

Protective Coating Action

Soothing Relief for 5 Symptoms:

Heartburn

Indigestion

Upset Stomach

Nausea

Diarrhea